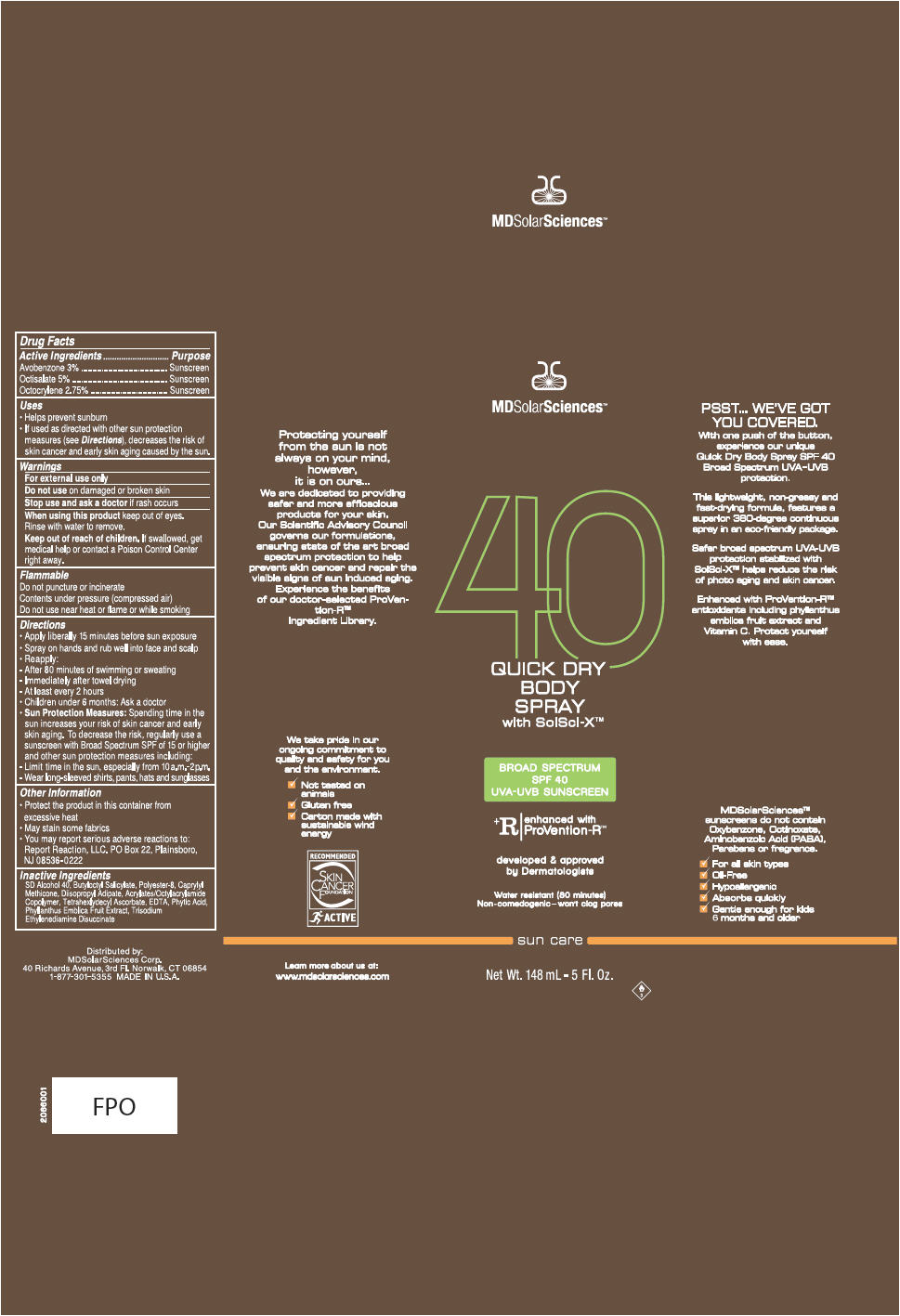 DRUG LABEL: Quick Dry Body
NDC: 49358-556 | Form: SPRAY
Manufacturer: MDSolarSciences
Category: otc | Type: HUMAN OTC DRUG LABEL
Date: 20250605

ACTIVE INGREDIENTS: AVOBENZONE 3 g/100 g; OCTISALATE 5 g/100 g; OCTOCRYLENE 2.75 g/100 g
INACTIVE INGREDIENTS: ALCOHOL; BUTYLOCTYL SALICYLATE; POLYESTER-8 (1400 MW, CYANODIPHENYLPROPENOYL CAPPED); CAPRYLYL TRISILOXANE; DIISOPROPYL ADIPATE; CARBOMER COPOLYMER TYPE A (ALLYL PENTAERYTHRITOL CROSSLINKED); EDETIC ACID; FYTIC ACID; PHYLLANTHUS EMBLICA FRUIT; TETRAHEXYLDECYL ASCORBATE; TRISODIUM ETHYLENEDIAMINE DISUCCINATE

Quick Dry Body Spray 5Fl Oz
Broad Spectrum SPF40 Sunscreen UVA-UVB Sunscreen with SolSci-X™

Drug Facts

ACTIVE INGREDIENT

Active Ingredients | Purpose
Avobenzone 3% | Sunscreen
Octisalate 5% | Sunscreen
Octocrylene 2.75% | Sunscreen

Uses

- Helps prevent sunburn
- If used as directed with other sun protection measures (see Directions), decreases the risk of skin cancer and early skin aging caused by the sun.

Warnings

For external use only

WHEN USING

When using this productavoid spraying in eyes. Rinse with water to remove.

Do not useon damaged or broken skin

Stop use and ask a doctorif rash or irritation develops and lasts.

Keep out of reach of children.If swallowed, get medical help or contact a Poison Control Center right away.

Flammable

Do not puncture or incinerate

Contents under pressure (compressed air)

Do not use near heat or flame or while smoking

Directions

- Apply liberally 15 minutes before sun exposure
- Spray on hands and rub well into face and scalp
- Reapply:
  - After 80 minutes of swimming or sweating
  - Immediately after towel drying
  - At least every 2 hours
- Children under 6 months: Ask a doctor
- Sun Protection Measures:Spending time in the sun increases your risk of skin cancer and early skin aging. To decrease the risk, regularly use a sunscreen with Broad Spectrum SPF of 15 or higher and other sun protection measures including:
  - Limit time in the sun, especially from 10a.m. – 2p.m.
  - Wear long-sleeved shirts, pants, hats and sunglasses.

Other Information

- Protect the product in this container from excessive heat
- May stain some fabrics
- You may report serious adverse reactions to Report Reaction, LLC. PO Box 22, Plainsboro, NJ 08536-0222

Inactive ingredients

SD Alcohol 40, Butyloctyl Salicylate, Polyester-8, Caprylyl Methicone, Diisopropyl Adipate, Acrylates/Octylacrylamide Copolymer, Tetrahexlydecyl Ascorbate, EDTA, Phytic Acid, Phyllanthus Emblica Fruit Extract, Trisodium Ethylenediamine Disuccinate

Distributed by:
MDSolarSciences Corp.
40 Richards Avenue, 3rd Fl., Norwalk, CT 06854

PRINCIPAL DISPLAY PANEL - 148 mL Can Carton

MDSolar Sciences™

40
QUICK DRY
BODY
SPRAY
with SolSci-X ™

BROAD SPECTRUM
SPF 40
UVA-UVB SUNSCREEN

^+R
enhanced with
ProVention-R ™

developed & approved
by Dermatologists

Water resistant (80 minutes)
Non-comedogenic – won't clog pores

sun care

Net Wt. 148 mL - 5 Fl. Oz.